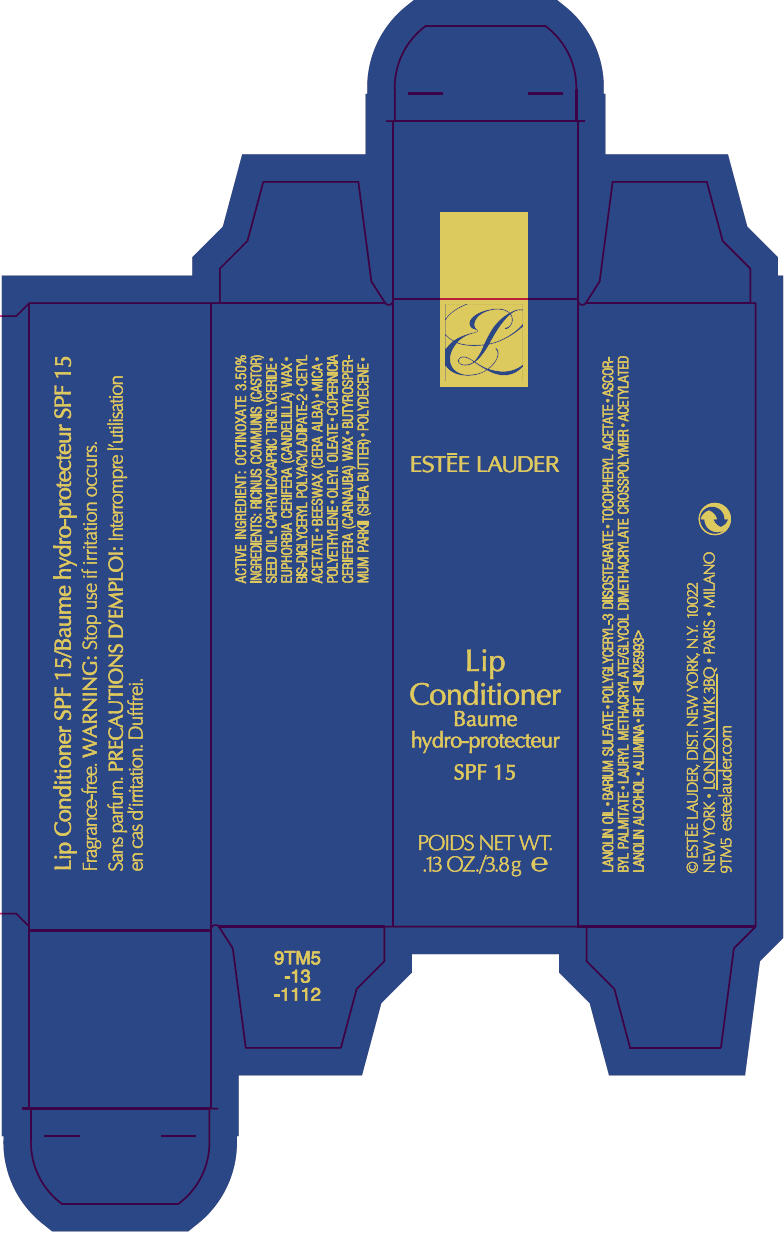 DRUG LABEL: LIP CONDITIONER SPF 15
NDC: 11559-725 | Form: LIPSTICK
Manufacturer: ESTEE LAUDER INC
Category: otc | Type: HUMAN OTC DRUG LABEL
Date: 20120302

ACTIVE INGREDIENTS: OCTINOXATE 3.5 g/100 g
INACTIVE INGREDIENTS: CASTOR OIL; MEDIUM-CHAIN TRIGLYCERIDES; CANDELILLA WAX; CETYL ACETATE; YELLOW WAX; MICA; HIGH DENSITY POLYETHYLENE; OLEYL OLEATE; CARNAUBA WAX; SHEA BUTTER; LANOLIN OIL; BARIUM SULFATE; POLYGLYCERYL-3 DIISOSTEARATE; .ALPHA.-TOCOPHEROL ACETATE; ASCORBYL PALMITATE; ALUMINUM OXIDE; BUTYLATED HYDROXYTOLUENE

Lip Conditioner SPF 15

WARNING

Stop use if irritation occurs.

ACTIVE INGREDIENT

OCTINOXATE 3.50%

INGREDIENTS

RICINUS COMMUNIS (CASTOR) SEED OIL • CAPRYLIC/CAPRIC TRIGLYCERIDE • EUPHORBIA CERIFERA (CANDELILLA) WAX • BIS-DIGLYCERYL POLYACYLADIPATE-2 • CETYL ACETATE • BEESWAX (CERA ALBA) • MICA • POLYETHYLENE • OLEYL OLEATE • COPERNICIA CERIFERA (CARNAUBA) WAX • BUTYROSPERMUM PARKII (SHEA BUTTER) • POLYDECENE • LANOLIN OIL • BARIUM SULFATE • POLYGLYCERYL-3 DIISOSTEARATE • TOCOPHERYL ACETATE • ASCORBYL PALMITATE • LAURYL METHACRYLATE/GLYCOL DIMETHACRYLATE CROSSPOLYMER • ACETYLATED LANOLIN ALCOHOL • ALUMINA • BHT <ILN25993>

©ESTĒE LAUDER, DIST. NEW YORK, N.Y. 10022

PRINCIPAL DISPLAY PANEL - 3.8 g Lipstick Carton

EL

ESTĒE LAUDER

Lip
Conditioner

SPF 15

NET WT.
.13 OZ./3.8 g e